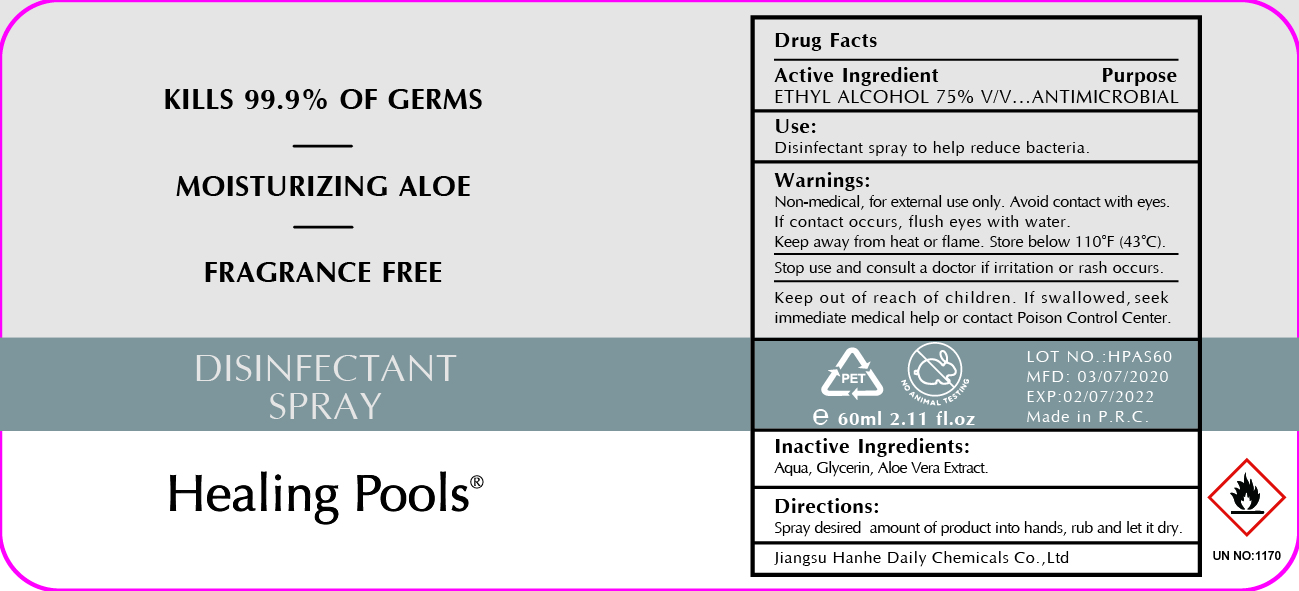 DRUG LABEL: Healing Pools Moisturizing Aloe Disinfectant
NDC: 73027-213 | Form: SPRAY
Manufacturer: JIANGSU HANHE DAILY CHEMICALS CO., LTD.
Category: otc | Type: HUMAN OTC DRUG LABEL
Date: 20211102

ACTIVE INGREDIENTS: ALCOHOL 75 mL/100 mL
INACTIVE INGREDIENTS: GLYCERIN; ALOE VERA WHOLE; WATER

-213 healing pools

ACTIVE INGREDIENT

Ethyl Alcohol 75% v/v

Purpose

Antimicrobial

Use

Disinfectant spray to help reduce bacteria

Warnings

Non Medical. For external use only.

Flammable. Keep away from heat or flame

Avoid contact with eyes. If contact occurs, flush eyes with water

Stop use and consult a doctor if irritation or rash occurs.

Keep out of reach of children. If swallowed, seek immediate medical help or contact a poison control center

Directions

- Spray desired amount of products into hands, rub and let it dry

Other Information

Store below 110F (43C)

Inactive ingredients

Water, Glycerin, Aloe vera extraxt